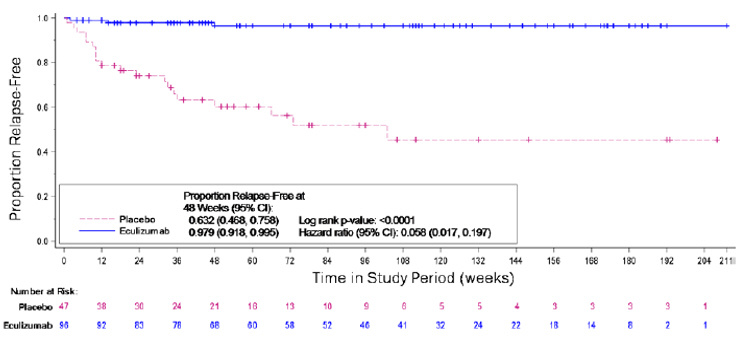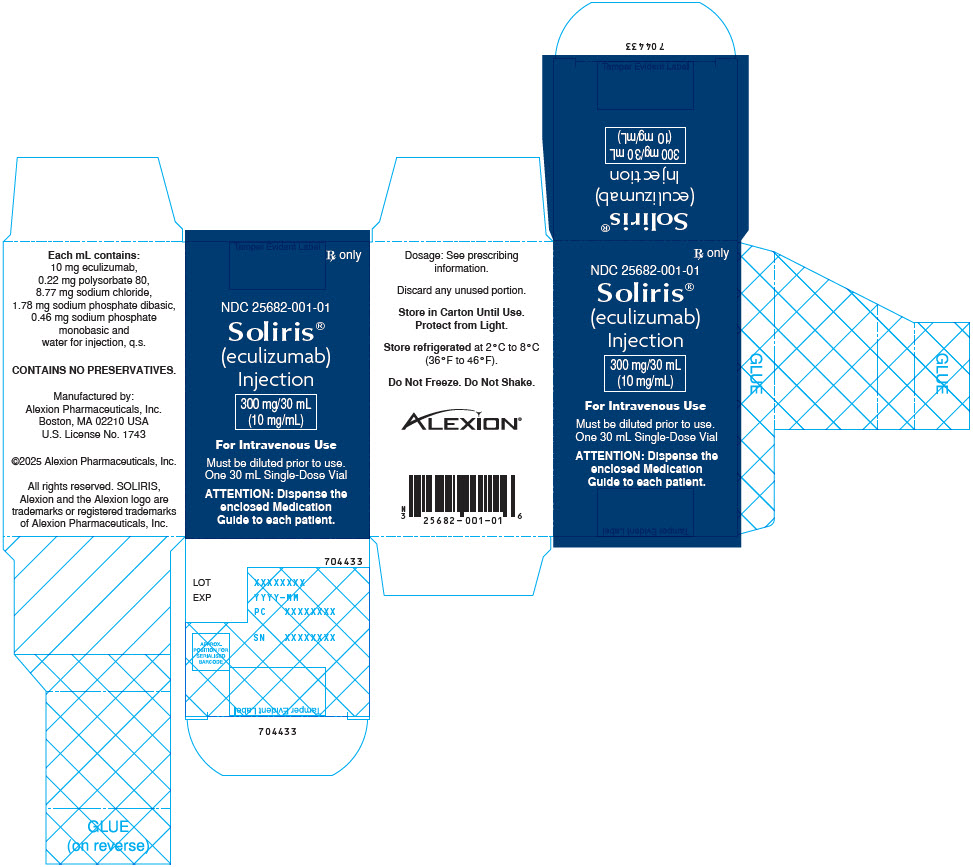 DRUG LABEL: SOLIRIS
NDC: 25682-001 | Form: INJECTION, SOLUTION, CONCENTRATE
Manufacturer: Alexion Pharmaceuticals Inc.
Category: prescription | Type: HUMAN PRESCRIPTION DRUG LABEL
Date: 20250307

ACTIVE INGREDIENTS: ECULIZUMAB 300 mg/30 mL
INACTIVE INGREDIENTS: SODIUM PHOSPHATE, MONOBASIC, UNSPECIFIED FORM; SODIUM PHOSPHATE, DIBASIC, UNSPECIFIED FORM; SODIUM CHLORIDE; POLYSORBATE 80; WATER

HIGHLIGHTS OF PRESCRIBING INFORMATION

These highlights do not include all the information needed to use SOLIRIS safely and effectively. See full prescribing information for SOLIRIS.
SOLIRIS® (eculizumab) injection, for intravenous use
Initial U.S. Approval: 2007

WARNING: SERIOUS MENINGOCOCCAL INFECTIONS

See full prescribing information for complete boxed warning

SOLIRIS increases the risk of serious and life-threatening infections caused by Neisseria meningitidis.

- Complete or update meningococcal vaccination at least 2 weeks prior to the first dose of SOLIRIS, unless the risks of delaying SOLIRIS outweigh the risk of developing a serious infection. Comply with the most current Advisory Committee on Immunization Practices (ACIP) recommendations for meningococcal vaccination in patients receiving a complement inhibitor. (5.1)
- Patients receiving SOLIRIS are at increased risk for invasive disease caused by N. meningitidis, even if they develop antibodies following vaccination. Monitor patients for early signs and symptoms of meningococcal infections, and evaluate immediately if infection is suspected. (5.1)

SOLIRIS is available only through a restricted program called the ULTOMIRIS and SOLIRIS REMS. (5.2)

RECENT MAJOR CHANGES

Boxed Warning | 03/2024
Indication and Usage (1.3) | 02/2025
Dosage and Administration (2.1) | 03/2024
Dosage and Administration (2.3, 2.4, 2.5) | 02/2025
Contraindications (4) | 03/2024
Warnings and Precautions (5.1) | 02/2024
Warnings and Precautions (5.2) | 03/2024

1 INDICATIONS AND USAGE

SOLIRIS is a complement inhibitor indicated for:

- the treatment of patients with paroxysmal nocturnal hemoglobinuria (PNH) to reduce hemolysis. (1.1)
- the treatment of patients with atypical hemolytic uremic syndrome (aHUS) to inhibit complement-mediated thrombotic microangiopathy. (1.2)
  Limitation of Use
  SOLIRIS is not indicated for the treatment of patients with Shiga toxin E. coli related hemolytic uremic syndrome (STEC-HUS).
- the treatment of generalized myasthenia gravis (gMG) in adult and pediatric patients six years of age and older who are anti-acetylcholine receptor (AChR) antibody positive. (1.3)
- the treatment of neuromyelitis optica spectrum disorder (NMOSD) in adult patients who are anti-aquaporin-4 (AQP4) antibody positive. (1.4)

2 DOSAGE AND ADMINISTRATION

For intravenous infusion only; recommended dosage for:

- PNH: (2.2)
- aHUS, gMG, and NMOSD in adults: (2.3)
- aHUS and gMG in pediatric patients: (2.4)

3 DOSAGE FORMS AND STRENGTHS

Injection: 300 mg/30 mL (10 mg/mL) in a single-dose vial. (3)

4 CONTRAINDICATIONS

SOLIRIS is contraindicated for initiation in patients with unresolved serious Neisseria meningitidis infection. (4)

5 WARNINGS AND PRECAUTIONS

- Use caution when administering SOLIRIS to patients with any other systemic infection. (5.3)
- Infusion-Related Reactions: Monitor patients during infusion, interrupt for reactions, and institute appropriate supportive measures. (5.6)

6 ADVERSE REACTIONS

The most frequently reported adverse reactions in the PNH randomized trial (≥10% overall and greater than placebo) are: headache, nasopharyngitis, back pain, and nausea. (6.1)

The most frequently reported adverse reactions in aHUS single arm prospective trials (≥20%) are: headache, diarrhea, hypertension, upper respiratory infection, abdominal pain, vomiting, nasopharyngitis, anemia, cough, peripheral edema, nausea, urinary tract infections, pyrexia. (6.1)

The most frequently reported adverse reaction in the gMG placebo-controlled clinical trial (≥10%) in adult patients is musculoskeletal pain. (6.1)

The most frequently reported adverse reactions in the NMOSD placebo- controlled trial (≥10%) are: upper respiratory infection, nasopharyngitis, diarrhea, back pain, dizziness, influenza, arthralgia, pharyngitis, and contusion. (6.1)

To report SUSPECTED ADVERSE REACTIONS, contact Alexion Pharmaceuticals, Inc. at 1-844-259-6783 or FDA at 1-800-FDA-1088 or www.fda.gov/medwatch.

FULL PRESCRIBING INFORMATION

WARNING: SERIOUS MENINGOCOCCAL INFECTIONS

SOLIRIS, a complement inhibitor, increases the risk of serious infections caused by Neisseria meningitidis [see Warnings and Precautions (5.1)]. Life-threatening and fatal meningococcal infections have occurred in patients treated with complement inhibitors. These infections may become rapidly life-threatening or fatal if not recognized and treated early.

- Complete or update vaccination for meningococcal bacteria (for serogroups A, C, W, Y, and B) at least 2 weeks prior to the first dose of SOLIRIS, unless the risks of delaying therapy with SOLIRIS outweigh the risk of developing a serious infection. Comply with the most current Advisory Committee on Immunization Practices (ACIP) recommendations for vaccinations against meningococcal bacteria in patients receiving a complement inhibitor. See Warnings and Precautions (5.1) for additional guidance on the management of the risk of serious infections caused by meningococcal bacteria.
- Patients receiving SOLIRIS are at increased risk for invasive disease caused by Neisseria meningitidis, even if they develop antibodies following vaccination. Monitor patients for early signs and symptoms of serious meningococcal infections and evaluate immediately if infection is suspected.

Because of the risk of serious meningococcal infections, SOLIRIS is available only through a restricted program under a Risk Evaluation and Mitigation Strategy (REMS) called ULTOMIRIS and SOLIRIS REMS [see Warnings and Precautions (5.2)].

1 INDICATIONS AND USAGE

1.1 Paroxysmal Nocturnal Hemoglobinuria (PNH)

SOLIRIS is indicated for the treatment of patients with paroxysmal nocturnal hemoglobinuria (PNH) to reduce hemolysis.

1.2 Atypical Hemolytic Uremic Syndrome (aHUS)

SOLIRIS is indicated for the treatment of patients with atypical hemolytic uremic syndrome (aHUS) to inhibit complement-mediated thrombotic microangiopathy.

Limitation of Use

SOLIRIS is not indicated for the treatment of patients with Shiga toxin E. coli related hemolytic uremic syndrome (STEC-HUS).

1.3 Generalized Myasthenia Gravis (gMG)

SOLIRIS is indicated for the treatment of generalized myasthenia gravis (gMG) in adult and pediatric patients six years of age and older who are anti-acetylcholine receptor (AChR) antibody positive.

1.4 Neuromyelitis Optica Spectrum Disorder (NMOSD)

SOLIRIS is indicated for the treatment of neuromyelitis optica spectrum disorder (NMOSD) in adult patients who are anti-aquaporin-4 (AQP4) antibody positive.

2 DOSAGE AND ADMINISTRATION

2.1 Recommended Vaccination and Prophylaxis for Meningococcal Infection

Vaccinate patients against meningococcal infection (serogroups A, C, W, Y and B) according to current ACIP recommendations at least 2 weeks prior to initiation of SOLIRIS [see Warnings and Precautions (5.1)].

If urgent SOLIRIS therapy is indicated in a patient who is not up to date with meningococcal vaccines according to ACIP recommendations, provide the patient with antibacterial drug prophylaxis and administer these vaccines as soon as possible.

Healthcare providers who prescribe SOLIRIS must enroll in the ULTOMIRIS and SOLIRIS REMS [see Warnings and Precautions (5.2)].

2.2 Recommended Dosage for Adults – PNH

The recommended dosage of SOLIRIS for the treatment of PNH in patients 18 years of age and older is administered as an intravenous infusion [see Dosage and Administration (2.7)] as follows:

- 600 mg weekly for the first 4 weeks, followed by
- 900 mg for the fifth dose 1 week later, then
- 900 mg every 2 weeks thereafter.

Administer SOLIRIS at the recommended dosage regimen time points, or within two days of these time points [see Warnings and Precautions (5.4)].

2.3 Recommended Dosage for Adults – aHUS, gMG, and NMOSD

The recommended dosage of SOLIRIS for the treatment of aHUS, gMG, or NMOSD in patients 18 years of age and older is administered as an intravenous infusion [see Dosage and Administration (2.7)] as follows:

- 900 mg weekly for the first 4 weeks, followed by
- 1200 mg for the fifth dose 1 week later, then
- 1200 mg every 2 weeks thereafter.

2.4 Recommended Dosage for Pediatric Patients – aHUS and gMG

The recommended dosage of SOLIRIS for the treatment of aHUS in pediatric patients less than 18 years of age or gMG in pediatric patients 6 years of age and older is administered as an intravenous infusion based upon body weight, according to the following schedule (Table 1):

Table 1: Dosing Recommendations in Pediatric Patients Less Than 18 Years of Age with aHUS and Pediatric Patients 6 Years of Age and Older with gMG
Patient Body Weight | Induction | Maintenance
40 kg and over | 900 mg weekly for the first 4 weeks | 1200 mg at week 5; then 1200 mg every 2 weeks
30 kg to less than 40 kg | 600 mg for the first 2 weeks | 900 mg at week 3; then 900 mg every 2 weeks
20 kg to less than 30 kg | 600 mg for the first 2 weeks | 600 mg at week 3; then 600 mg every 2 weeks
10 kg to less than 20 kg | 600 mg single dose at Week 1 | 300 mg at week 2; then 300 mg every 2 weeks
5 kg to less than 10 kg | 300 mg single dose at Week 1 | 300 mg at week 2; then 300 mg every 3 weeks

Administer SOLIRIS at the recommended dosage regimen time points, or within two days of these time points.

2.5 Dose Adjustment in Case of Plasmapheresis, Plasma Exchange, Fresh Frozen Plasma Infusion or IVIg

For adult and pediatric patients with aHUS or gMG, and adult patients with NMOSD, supplemental dosing of SOLIRIS is required in the setting of concomitant plasmapheresis or plasma exchange, or fresh frozen plasma infusion (PE/PI) (Table 2).

Table 2: Supplemental Dose of SOLIRIS after Plasmapheresis/PE/PI
Type of Plasma Intervention | Most Recent SOLIRIS Dose | Supplemental SOLIRIS Dose with Each Plasma Intervention | Timing of Supplemental SOLIRIS Dose
Plasmapheresis or plasma exchange | 300 mg | 300 mg per each plasmapheresis or plasma exchange session | Within 60 minutes after each plasmapheresis or plasma exchange
Plasmapheresis or plasma exchange | ≥600 mg | 600 mg per each plasmapheresis or plasma exchange session | Within 60 minutes after each plasmapheresis or plasma exchange
Fresh frozen plasma infusion | ≥300 mg | 300 mg per infusion of fresh frozen plasma | 60 minutes prior to each infusion of fresh frozen plasma

For patients with gMG, a supplemental dose of SOLIRIS is required in the setting of concomitant use of intravenous immunoglobulin (IVIg) treatment as described in Table 3.

Table 3: Supplemental Dose of SOLIRIS with concomitant IVIg
IVIg Frequency | Most Recent SOLIRIS Dose | Supplemental Soliris Dose per IVIg Cycle | Timing of Supplemental SOLIRIS Dose
Acute rescue therapy | No supplemental SOLIRIS dose needed
Equal to or more frequent than every 4 weeks | 900 mg or more | 600 mg | At the same time as scheduled SOLIRIS dose
Equal to or more frequent than every 4 weeks | 600 mg or less | 300 mg | At the same time as scheduled SOLIRIS dose
Less frequent than every 4 weeks | 900 mg or more | 600 mg | At the next scheduled SOLIRIS dose after the last IVIg cycle
Less frequent than every 4 weeks | 600 mg or less | 300 mg | At the next scheduled SOLIRIS dose after the last IVIg cycle

2.6 Preparation

Dilute SOLIRIS to a final admixture concentration of 5 mg/mL using the following steps:

- Withdraw the required amount of SOLIRIS from the vial into a sterile syringe.
- Transfer the recommended dose to an infusion bag.
- Dilute SOLIRIS to a final concentration of 5 mg/mL by adding the appropriate amount (equal volume of diluent to drug volume) of 0.9% Sodium Chloride Injection, USP; 0.45% Sodium Chloride Injection, USP; 5% Dextrose in Water Injection, USP; or Ringer's Injection, USP to the infusion bag.

The final admixed SOLIRIS 5 mg/mL infusion volume is 60 mL for 300 mg doses, 120 mL for 600 mg doses, 180 mL for 900 mg doses or 240 mL for 1200 mg doses (Table 4).

Table 4: Preparation and Reconstitution of SOLIRIS
SOLIRIS Dose | Diluent Volume | Final Volume
300 mg | 30 mL | 60 mL
600 mg | 60 mL | 120 mL
900 mg | 90 mL | 180 mL
1200 mg | 120 mL | 240 mL

Gently invert the infusion bag containing the diluted SOLIRIS solution to ensure thorough mixing of the product and diluent. Discard any unused portion left in a vial, as the product contains no preservatives.

Prior to administration, the admixture should be allowed to adjust to room temperature [18°C to 25°C, 64°F to 77°F]. The admixture must not be heated in a microwave or with any heat source other than ambient air temperature.

Parenteral drug products should be inspected visually for particulate matter and discoloration prior to administration, whenever solution and container permit.

2.7 Administration

Only administer as an intravenous infusion.

Do not administer as an intravenous push or bolus injection.

Administer the SOLIRIS admixture by intravenous infusion over 35 minutes in adults and 1 to 4 hours in pediatric patients via gravity feed, a syringe-type pump, or an infusion pump. Admixed solutions of SOLIRIS are stable for 24 h at 2°C to 8°C (36°F to 46°F) and at room temperature.

If an adverse reaction occurs during the administration of SOLIRIS, the infusion may be slowed or stopped at the discretion of the physician. If the infusion is slowed, the total infusion time should not exceed two hours in adults. Monitor the patient for at least one hour following completion of the infusion for signs or symptoms of an infusion-related reaction.

3 DOSAGE FORMS AND STRENGTHS

Injection: 300 mg/30 mL (10 mg/mL) as a clear, colorless solution in a single-dose vial.

4 CONTRAINDICATIONS

SOLIRIS is contraindicated for initiation in patients with unresolved serious Neisseria meningitidis infection [see Warnings and Precautions (5.1)].

5 WARNINGS AND PRECAUTIONS

5.1 Serious Meningococcal Infections

SOLIRIS, a complement inhibitor, increases a patient's susceptibility to serious, life-threatening, or fatal infections caused by meningococcal bacteria (septicemia and/or meningitis) in any serogroup, including non-groupable strains. Life-threatening and fatal meningococcal infections have occurred in both vaccinated and unvaccinated patients treated with complement inhibitors. The initiation of SOLIRIS treatment is contraindicated in patients with unresolved serious Neisseria meningitidis infection.

Complete or update meningococcal vaccination (for serogroups A, C, W, Y and B) at least 2 weeks prior to administration of the first dose of SOLIRIS, according to current ACIP recommendations for patients receiving a complement inhibitor. Revaccinate patients in accordance with ACIP recommendations, considering the duration of therapy with SOLIRIS. Note that ACIP recommends an administration schedule in patients receiving complement inhibitors that differs from the administration schedule in the vaccine prescribing information. If urgent SOLIRIS therapy is indicated in a patient who is not up to date with meningococcal vaccines according to ACIP recommendations, provide the patient with antibacterial drug prophylaxis and administer meningococcal vaccines as soon as possible. Various durations and regimens of antibacterial drug prophylaxis have been considered, but the optimal durations and drug regimens for prophylaxis and their efficacy have not been studied in unvaccinated or vaccinated patients receiving complement inhibitors, including SOLIRIS. The benefits and risks of treatment with SOLIRIS, as well as the benefits and risks of antibacterial drug prophylaxis in unvaccinated or vaccinated patients, must be considered against the known risks for serious infections caused by Neisseria meningitidis.

Vaccination does not eliminate the risk of serious meningococcal infections, despite development of antibodies following vaccination.

Closely monitor patients for early signs and symptoms of meningococcal infection and evaluate patients immediately if infection is suspected. Inform patients of these signs and symptoms and instruct patients to seek immediate medical care if these signs and symptoms occur. Promptly treat known infections. Meningococcal infection may become rapidly life-threatening or fatal if not recognized and treated early. Consider interruption of SOLIRIS in patients who are undergoing treatment for serious meningococcal infection depending on the risks of interrupting treatment in the disease being treated.

SOLIRIS is available only through a restricted program under a REMS [see Warnings and Precautions (5.2)].

5.2 ULTOMIRIS and SOLIRIS REMS

SOLIRIS is available only through a restricted program under a REMS called ULTOMIRIS and SOLIRIS REMS, because of the risk of serious meningococcal infections [see Warnings and Precautions (5.1)].

Notable requirements of the ULTOMIRIS and SOLIRIS REMS include the following:

- Prescribers must enroll in the REMS.
- Prescribers must counsel patients about the risk of serious meningococcal infection.
- Prescribers must provide the patients with the REMS educational materials.
- Prescribers must assess patient vaccination status for meningococcal vaccines (against serogroups A, C, W, Y and B) and vaccinate if needed according to current ACIP recommendations two weeks prior to the first dose of SOLIRIS.
- Prescribers must provide a prescription for antibacterial drug prophylaxis if treatment must be started urgently and the patient is not up to date with meningococcal vaccines according to current ACIP recommendations at least two weeks prior to the first dose of SOLIRIS.
- Healthcare settings and pharmacies that dispense SOLIRIS must be certified in the REMS and must verify prescribers are certified.
- Patients must receive counseling from the prescriber about the need to receive meningococcal vaccines per ACIP recommendations, the need to take antibiotics as directed by the prescriber, and the signs and symptoms of meningococcal infection.
- Patients must be instructed to carry the Patient Safety Card with them at all times during and for 3 months following treatment with SOLIRIS.

Further information is available at www.UltSolREMS.com or 1-888-765-4747.

5.3 Other Infections

Serious infections with Neisseria species (other than Neisseria meningitidis), including disseminated gonococcal infections, have been reported.

SOLIRIS blocks terminal complement activation; therefore patients may have increased susceptibility to infections, especially with encapsulated bacteria such as infections with Neisseria meningitidis but also Streptococcus pneumoniae, Haemophilus influenzae, and to a lesser extent, Neisseria gonorrhoeae. Additionally, Aspergillus infections have occurred in immunocompromised and neutropenic patients. Children treated with SOLIRIS may be at increased risk of developing serious infections due to Streptococcus pneumoniae and Haemophilus influenzae type b (Hib). Administer vaccinations for the prevention of Streptococcus pneumoniae and Haemophilus influenzae type b (Hib) infections according to ACIP recommendations. Patients receiving SOLIRIS are at increased risk for infections due to these organisms, even if they develop antibodies following vaccination.

5.4 Monitoring Disease Manifestations after SOLIRIS Discontinuation

Treatment Discontinuation for PNH

Monitor patients after discontinuing SOLIRIS for at least 8 weeks to detect hemolysis.

Treatment Discontinuation for aHUS

After discontinuing SOLIRIS, monitor patients with aHUS for signs and symptoms of thrombotic microangiopathy (TMA) complications for at least 12 weeks. In aHUS clinical trials, 18 patients (5 in the prospective studies) discontinued SOLIRIS treatment. TMA complications occurred following a missed dose in 5 patients, and SOLIRIS was reinitiated in 4 of these 5 patients.

Clinical signs and symptoms of TMA include changes in mental status, seizures, angina, dyspnea, or thrombosis. In addition, the following changes in laboratory parameters may identify a TMA complication: occurrence of two, or repeated measurement of any one of the following: a decrease in platelet count by 25% or more compared to baseline or the peak platelet count during SOLIRIS treatment; an increase in serum creatinine by 25% or more compared to baseline or nadir during SOLIRIS treatment; or, an increase in serum LDH by 25% or more over baseline or nadir during SOLIRIS treatment.

If TMA complications occur after SOLIRIS discontinuation, consider reinstitution of SOLIRIS treatment, plasma therapy [plasmapheresis, plasma exchange, or fresh frozen plasma infusion (PE/PI)], or appropriate organ-specific supportive measures.

5.5 Thrombosis Prevention and Management

The effect of withdrawal of anticoagulant therapy during SOLIRIS treatment has not been established. Therefore, treatment with SOLIRIS should not alter anticoagulant management.

5.6 Infusion-Related Reactions

Administration of SOLIRIS may result in infusion-related reactions, including anaphylaxis or other hypersensitivity reactions. In clinical trials, no patients experienced an infusion-related reaction which required discontinuation of SOLIRIS. Interrupt SOLIRIS infusion and institute appropriate supportive measures if signs of cardiovascular instability or respiratory compromise occur.

6 ADVERSE REACTIONS

The following serious adverse reactions are discussed in greater detail in other sections of the labeling:

- Serious Meningococcal Infections [see Warnings and Precautions (5.1)]
- Other Infections [see Warnings and Precautions (5.3)]
- Monitoring Disease Manifestations after SOLIRIS Discontinuation [see Warnings and Precautions (5.4)]
- Thrombosis Prevention and Management [see Warnings and Precautions (5.5)]
- Infusion-Related Reactions [see Warnings and Precautions (5.6)]

6.1 Clinical Trial Experience

Because clinical trials are conducted under widely varying conditions, adverse reaction rates observed in the clinical trials of a drug cannot be directly compared to rates in the clinical trials of another drug and may not reflect the rates observed in practice.

Meningococcal infections are the most important adverse reactions experienced by patients receiving SOLIRIS. In PNH clinical studies, two patients experienced meningococcal sepsis. Both patients had previously received a meningococcal vaccine. In clinical studies among patients without PNH, meningococcal meningitis occurred in one unvaccinated patient. Meningococcal sepsis occurred in one previously vaccinated patient enrolled in the retrospective aHUS study during the post-study follow-up period [see Warnings and Precautions (5.1)].

PNH

The data described below reflect exposure to SOLIRIS in 196 adult patients with PNH, age 18-85, of whom 55% were female. All had signs or symptoms of intravascular hemolysis. SOLIRIS was studied in a placebo-controlled clinical study (PNH Study 1, in which 43 patients received SOLIRIS and 44, placebo); a single arm clinical study (PNH Study 2); and a long term extension study (E05-001). 182 patients were exposed for greater than one year. All patients received the recommended SOLIRIS dose regimen.

Table 5 summarizes the adverse reactions that occurred at a numerically higher rate in the SOLIRIS group than the placebo group and at a rate of 5% or more among patients treated with SOLIRIS.

Table 5: Adverse Reactions Reported in 5% or More of SOLIRIS Treated Patients with PNH and Greater than Placebo in the Controlled Clinical Study
Reaction | SOLIRIS (N=43) N (%) | Placebo (N=44) N (%)
Headache | 19 (44) | 12 (27)
Nasopharyngitis | 10 (23) | 8 (18)
Back pain | 8 (19) | 4 (9)
Nausea | 7 (16) | 5 (11)
Fatigue | 5 (12) | 1 (2)
Cough | 5 (12) | 4 (9)
Herpes simplex infections | 3 (7) | 0
Sinusitis | 3 (7) | 0
Respiratory tract infection | 3 (7) | 1 (2)
Constipation | 3 (7) | 2 (5)
Myalgia | 3 (7) | 1 (2)
Pain in extremity | 3 (7) | 1 (2)
Influenza-like illness | 2 (5) | 1 (2)

In the placebo-controlled clinical study, serious adverse reactions occurred among 4 (9%) patients receiving SOLIRIS and 9 (21%) patients receiving placebo. The serious reactions included infections and progression of PNH. No deaths occurred in the study and no patients receiving SOLIRIS experienced a thrombotic event; one thrombotic event occurred in a patient receiving placebo.

Among 193 patients with PNH treated with SOLIRIS in the single arm, clinical study or the follow-up study, the adverse reactions were similar to those reported in the placebo-controlled clinical study. Serious adverse reactions occurred among 16% of the patients in these studies. The most common serious adverse reactions were: viral infection (2%), headache (2%), anemia (2%), and pyrexia (2%).

aHUS

The safety of SOLIRIS therapy in patients with aHUS was evaluated in four prospective, single-arm studies, three in adult and adolescent patients (Studies C08-002A/B, C08-003A/B, and C10-004), one in pediatric and adolescent patients (Study C10-003), and one retrospective study (Study C09-001r).

The data described below were derived from 78 adult and adolescent patients with aHUS in Studies C08-002A/B, C08-003A/B and C10-004. All patients received the recommended dosage of SOLIRIS. Median exposure was 67 weeks (range: 2-145 weeks). Table 6 summarizes all adverse events reported in at least 10% of patients in Studies C08-002A/B, C08-003A/B and C10-004 combined.

Table 6: Per Patient Incidence of Adverse Events in 10% or More Adult and Adolescent Patients Enrolled in Studies C08-002A/B, C08-003A/B and C10-004 Separately and in Total
 |  | Number (%) of Patients
 | C08-002A/B (N=17) | C08-003A/B (N=20) | C10-004 (N=41) | Total (N=78)
Vascular Disorders
Hypertension [includes the preferred terms hypertension, accelerated hypertension, and malignant hypertension.] | 10 (59) | 9 (45) | 7 (17) | 26 (33)
Hypotension | 2 (12) | 4 (20) | 7 (17) | 13 (17)
Infections and Infestations
Bronchitis | 3 (18) | 2 (10) | 4 (10) | 9 (12)
Nasopharyngitis | 3 (18) | 11 (55) | 7 (17) | 21 (27)
Gastroenteritis | 3 (18) | 4 (20) | 2 (5) | 9 (12)
Upper respiratory tract infection | 5 (29) | 8 (40) | 2 (5) | 15 (19)
Urinary tract infection | 6 (35) | 3 (15) | 8 (20) | 17 (22)
Gastrointestinal Disorders
Diarrhea | 8 (47) | 8 (40) | 12 (32) | 29 (37)
Vomiting | 8 (47) | 9 (45) | 6 (15) | 23 (30)
Nausea | 5 (29) | 8 (40) | 5 (12) | 18 (23)
Abdominal pain | 3 (18) | 6 (30) | 6 (15) | 15 (19)
Nervous System Disorders
Headache | 7 (41) | 10 (50) | 15 (37) | 32 (41)
Blood and Lymphatic System Disorders
Anemia | 6 (35) | 7 (35) | 7 (17) | 20 (26)
Leukopenia | 4 (24) | 3 (15) | 5 (12) | 12 (15)
Psychiatric Disorders
Insomnia | 4 (24) | 2 (10) | 5 (12) | 11 (14)
Renal and Urinary Disorders
Renal Impairment | 5 (29) | 3 (15) | 6 (15) | 14 (18)
Proteinuria | 2 (12) | 1 (5) | 5 (12) | 8 (10)
Respiratory, Thoracic and Mediastinal Disorders
Cough | 4 (24) | 6 (30) | 8 (20) | 18 (23)
General Disorders and Administration Site Conditions
Fatigue | 3 (18) | 4 (20) | 3 (7) | 10 (13)
Peripheral edema | 5 (29) | 4 (20) | 9 (22) | 18 (23)
Pyrexia | 4 (24) | 5 (25) | 7 (17) | 16 (21)
Asthenia | 3 (18) | 4 (20) | 6 (15) | 13 (17)
Eye Disorder | 5 (29) | 2 (10) | 8 (20) | 15 (19)
Metabolism and Nutrition Disorders
Hypokalemia | 3 (18) | 2 (10) | 4 (10) | 9 (12)
Neoplasms benign, malignant, and unspecified (including cysts and polyps) | 1 (6) | 6 (30) | 1 (20) | 8 (10)
Skin and Subcutaneous Tissue Disorders
Rash | 2 (12) | 3 (15) | 6 (15) | 11 (14)
Pruritus | 1 (6) | 3 (15) | 4 (10) | 8 (10)
Musculoskeletal and Connective Tissue Disorders
Arthralgia | 1 (6) | 2 (10) | 7 (17) | 10 (13)
Back pain | 3 (18) | 3 (15) | 2 (5) | 8 (10)

In Studies C08-002A/B, C08-003A/B and C10-004 combined, 60% (47/78) of patients experienced a serious adverse event (SAE). The most commonly reported SAEs were infections (24%), hypertension (5%), chronic renal failure (5%), and renal impairment (5%). Five patients discontinued SOLIRIS due to adverse events; three due to worsening renal function, one due to new diagnosis of Systemic Lupus Erythematosus, and one due to meningococcal meningitis.

Study C10-003 included 22 pediatric and adolescent patients, of which 18 patients were less than 12 years of age. All patients received the recommended dosage of SOLIRIS. Median exposure was 44 weeks (range: 1 dose-87 weeks).

Table 7 summarizes all adverse events reported in at least 10% of patients enrolled in Study C10-003.

Table 7: Per Patient Incidence of Adverse Reactions in 10% or More Patients Enrolled in Study C10-003
 | 1 month to <12 yrs (N=18) | Total (N=22)
Eye Disorders | 3 (17) | 3 (14)
Gastrointestinal Disorders
Abdominal pain | 6 (33) | 7 (32)
Diarrhea | 5 (28) | 7 (32)
Vomiting | 4 (22) | 6 (27)
Dyspepsia | 0 | 3 (14)
General Disorders and Administration Site Conditions
Pyrexia | 9 (50) | 11 (50)
Infections and Infestations
Upper respiratory tract infection | 5 (28) | 7 (32)
Nasopharyngitis | 3 (17) | 6 (27)
Rhinitis | 4 (22) | 4 (18)
Urinary Tract infection | 3 (17) | 4 (18)
Catheter site infection | 3 (17) | 3 (14)
Musculoskeletal and Connective Tissue Disorders
Muscle spasms | 2 (11) | 3 (14)
Nervous System Disorders
Headache | 3 (17) | 4 (18)
Renal and Urinary Disorders | 3 (17) | 4 (18)
Respiratory, Thoracic and Mediastinal Disorders
Cough | 7 (39) | 8 (36)
Oropharyngeal pain | 1 (6) | 3 (14)
Skin and Subcutaneous Tissue Disorders
Rash | 4 (22) | 4 (18)
Vascular Disorders
Hypertension | 4 (22) | 4 (18)

In Study C10-003, 59% (13/22) of patients experienced a serious adverse event (SAE). The most commonly reported SAEs were hypertension (9%), viral gastroenteritis (9%), pyrexia (9%), and upper respiratory infection (9%). One patient discontinued SOLIRIS due to an adverse event (severe agitation).

Analysis of retrospectively collected adverse event data from pediatric and adult patients enrolled in Study C09-001r (N=30) revealed a safety profile that was similar to that which was observed in the two prospective studies. Study C09-001r included 19 pediatric patients less than 18 years of age. Overall, the safety of SOLIRIS in pediatric patients with aHUS enrolled in Study C09-001r appeared similar to that observed in adult patients. The most common (≥15%) adverse events occurring in pediatric patients are presented in Table 8.

Table 8: Adverse Reactions Occurring in at Least 15% of Patients Less than 18 Years of Age Enrolled in Study C09-001r
 | Number (%) of Patients
 | < 2 yrs (N=5) | 2 to < 12 yrs (N=10) | 12 to <18 yrs (N=4) | Total (N=19)
General Disorders and Administration Site Conditions
Pyrexia | 4 (80) | 4 (40) | 1 (25) | 9 (47)
Gastrointestinal Disorders
Diarrhea | 1 (20) | 4 (40) | 1 (25) | 6 (32)
Vomiting | 2 (40) | 1 (10) | 1 (25) | 4 (21)
Infections and Infestations
Upper respiratory tract infection [includes the preferred terms upper respiratory tract infection and nasopharyngitis.] | 2 (40) | 3 (30) | 1 (25) | 6 (32)
Respiratory, Thoracic and Mediastinal Disorders
Cough | 3 (60) | 2 (20) | 0 (0) | 5 (26)
Nasal congestion | 2 (40) | 2 (20) | 0 (0) | 4 (21)
Cardiac Disorders
Tachycardia | 2 (40) | 2 (20) | 0 (0) | 4 (21)

Generalized Myasthenia Gravis (gMG)

Adults

In a 26-week placebo-controlled trial evaluating the effect of SOLIRIS for the treatment of adult patients with gMG (Study ECU-MG-301), 62 patients received SOLIRIS at the recommended dosage regimen and 63 patients received placebo [see Clinical Studies (14.3)]. Patients were 19 to 79 years of age, and 66% were female. Table 9 displays the most common adverse reactions from gMG Study 1 that occurred in ≥5% of SOLIRIS-treated patients and at a greater frequency than on placebo.

Table 9: Adverse Reactions Reported in 5% or More of SOLIRIS-Treated Patients in Study ECU-MG-301 and at a Greater Frequency than in Placebo-Treated Patients
 | SOLIRIS (N=62) N (%) | Placebo (N=63) N (%)
Gastrointestinal Disorders
Abdominal pain | 5 (8) | 3 (5)
General Disorders and Administration Site Conditions
Peripheral edema | 5 (8) | 3 (5)
Pyrexia | 4 (7) | 2 (3)
Infections and Infestations
Herpes simplex virus infections | 5 (8) | 1 (2)
Injury, Poisoning, and Procedural Complications
Contusion | 5 (8) | 2 (3)
Musculoskeletal and Connective Tissue Disorders
Musculoskeletal pain | 9 (15) | 5 (8)

The most common adverse reactions (≥10%) that occurred in SOLIRIS-treated patients in the long-term extension to Study ECU-MG-301, Study ECU-MG-302, and that are not included in Table 9 were headache (26%), nasopharyngitis (24%), diarrhea (15%), arthralgia (12%), upper respiratory tract infection (11%), and nausea (10%).

Pediatric Patients 6 Years of Age and Older

In a 26-week, single arm study evaluating the safety of SOLIRIS in 11 pediatric patients with gMG 12 to 17 years of age (Study ECU-MG-303), adverse reactions were consistent with those observed in adult patients with gMG [see Use in Specific Populations (8.4)]. The safety of SOLIRIS in pediatric patients 6 to less than 12 years of age is expected to be similar to that of adults and pediatric patients 12 years of age and older treated with SOLIRIS.

Neuromyelitis Optica Spectrum Disorder (NMOSD)

In a placebo-controlled trial evaluating the effect of SOLIRIS for the treatment of NMOSD (NMOSD Study 1), 96 patients received SOLIRIS at the recommended dosage regimen and 47 patients received placebo [see Clinical Studies (14.4)]. Patients were 19 to 75 years of age (mean 44 years of age), and 91% were female. Table 10 displays the most common adverse reactions from NMOSD Study 1 that occurred in ≥5% of SOLIRIS-treated patients and at a greater frequency than on placebo.

Table 10: Adverse Reactions Reported in 5% or More of SOLIRIS-Treated Patients in NMOSD Study 1 and at a Greater Frequency than in Placebo-Treated Patients
 | SOLIRIS (N=96) N (%) | Placebo (N=47) N (%)
Events/Patients | 1295/88 | 617/45
Blood and lymphatic system disorders
Leukopenia | 5 (5) | 1 (2)
Lymphopenia | 5 (5) | 0 (0)
Eye disorders
Cataract | 6 (6) | 2 (4)
Gastrointestinal disorders
Diarrhea | 15 (16) | 7 (15)
Constipation | 9 (9) | 3 (6)
General disorders and administration site conditions
Asthenia | 5 (5) | 1 (2)
Infections and infestations
Upper respiratory tract infection | 28 (29) | 6 (13)
Nasopharyngitis | 20 (21) | 9 (19)
Influenza | 11 (11) | 2 (4)
Pharyngitis | 10 (10) | 3 (6)
Bronchitis | 9 (9) | 3 (6)
Conjunctivitis | 9 (9) | 4 (9)
Cystitis | 8 (8) | 1 (2)
Hordeolum | 7 (7) | 0 (0)
Sinusitis | 6 (6) | 0 (0)
Cellulitis | 5 (5) | 1 (2)
Injury, poisoning and procedural complications
Contusion | 10 (10) | 2 (4)
Metabolism and nutrition disorders
Decreased appetite | 5 (5) | 1 (2)
Musculoskeletal and connective tissue disorders
Back pain | 14 (15) | 6 (13)
Arthralgia | 11 (11) | 5 (11)
Musculoskeletal pain | 6 (6) | 0 (0)
Muscle spasms | 5 (5) | 2 (4)
Nervous system disorders
Dizziness | 14 (15) | 6 (13)
Paraesthesia | 8 (8) | 3 (6)
Respiratory, thoracic and mediastinal disorders
Oropharyngeal pain | 7 (7) | 2 (4)
Skin and subcutaneous tissue disorders
Alopecia | 5 (5) | 2 (4)

6.2 Postmarketing Experience

The following adverse reactions have been identified during post-approval use of SOLIRIS. Because these reactions are reported voluntarily from a population of uncertain size, it is not always possible to reliably estimate their frequency or establish a causal relationship to SOLIRIS exposure.

Adverse Reactions from Postmarketing Spontaneous Reports

- Fatal or serious infections: Neisseria gonorrhoeae, Neisseria meningitidis, Neisseria sicca/subflava, Neisseria spp unspecified.
- Cases of cholestatic or mixed pattern liver injury with increased serum liver enzymes and bilirubin levels have been reported in adult and pediatric patients with aHUS who were treated with Soliris. These events occurred within 3 to 27 days after starting treatment. The median time to resolution (or return to baseline) was approximately 3 weeks.

7 DRUG INTERACTIONS

7.1 Plasmapheresis, Plasma Exchange, Fresh Frozen Plasma Infusion or IVIg

Concomitant use of SOLIRIS with plasma exchange (PE), plasmapheresis (PP) , fresh frozen plasma infusion (PE/PI), or in patients with gMG on concomitant IVIg treatment can reduce serum eculizumab concentrations and requires a supplemental dose of SOLIRIS [see Dosage and Administration (2.5)].

7.2 Neonatal Fc Receptor Blockers

Concomitant use of SOLIRIS with neonatal Fc receptor (FcRn) blockers may lower systemic exposures and reduce effectiveness of SOLIRIS. Closely monitor for reduced effectiveness of SOLIRIS.

8 USE IN SPECIFIC POPULATIONS

8.1 Pregnancy

Risk Summary

Limited data on outcomes of pregnancies that have occurred following SOLIRIS use in pregnant women have not identified a concern for specific adverse developmental outcomes (see Data). There are risks to the mother and fetus associated with untreated paroxysmal nocturnal hemoglobinuria (PNH) and atypical hemolytic uremic syndrome (aHUS) in pregnancy (see Clinical Considerations).

Animal studies using a mouse analogue of the SOLIRIS molecule (murine anti-C5 antibody) showed increased rates of developmental abnormalities and an increased rate of dead and moribund offspring at doses 2-8 times the human dose (see Data).

The estimated background risk of major birth defects and miscarriage for the indicated populations is unknown. All pregnancies have a background risk of birth defect, loss, or other adverse outcomes. In the U.S. general population, the estimated background risk of major birth defect and miscarriage in clinically recognized pregnancies is 2-4% and 15-20%, respectively.

Clinical Considerations

Disease-associated maternal and/or fetal/neonatal risk

PNH in pregnancy is associated with adverse maternal outcomes, including worsening cytopenias, thrombotic events, infections, bleeding, miscarriages and increased maternal mortality, and adverse fetal outcomes, including fetal death and premature delivery.

aHUS in pregnancy is associated with adverse maternal outcomes, including pre-eclampsia and preterm delivery, and adverse fetal/neonatal outcomes, including intrauterine growth restriction (IUGR), fetal death and low birth weight.

Data

Human Data

A pooled analysis of prospectively (50.3%) and retrospectively (49.7%) collected data in more than 300 pregnant women with live births following exposure to SOLIRIS have not suggested safety concerns. However, these data cannot definitively exclude any drug-associated risk during pregnancy, because of the limited sample size.

Animal Data

Animal reproduction studies were conducted in mice using doses of a murine anti-C5 antibody that approximated 2-4 times (low dose) and 4-8 times (high dose) the recommended human SOLIRIS dose, based on a body weight comparison. When animal exposure to the antibody occurred in the time period from before mating until early gestation, no decrease in fertility or reproductive performance was observed. When maternal exposure to the antibody occurred during organogenesis, two cases of retinal dysplasia and one case of umbilical hernia were observed among 230 offspring born to mothers exposed to the higher antibody dose; however, the exposure did not increase fetal loss or neonatal death. When maternal exposure to the antibody occurred in the time period from implantation through weaning, a higher number of male offspring became moribund or died (1/25 controls, 2/25 low dose group, 5/25 high dose group). Surviving offspring had normal development and reproductive function.

8.2 Lactation

Risk Summary

Although limited published data does not report detectable levels of eculizumab in human milk, maternal IgG is known to be present in human milk. Available information is insufficient to inform the effect of eculizumab on the breastfed infant. There are no data on the effects of eculizumab on milk production. The developmental and health benefits of breastfeeding should be considered along with the mother's clinical need for SOLIRIS and any potential adverse effects on the breastfed child from eculizumab or from the underlying maternal condition.

8.4 Pediatric Use

PNH and NMOSD

Safety and effectiveness of SOLIRIS for the treatment of PNH, or NMOSD in pediatric patients have not been established.

aHUS

The safety and effectiveness of SOLIRIS for the treatment of aHUS have been established in pediatric patients. Use of SOLIRIS in pediatric patients for this indication is supported by evidence from four adequate and well-controlled clinical studies assessing the safety and effectiveness of SOLIRIS for the treatment of aHUS. The studies included a total of 47 pediatric patients (ages 2 months to 17 years). The safety and effectiveness of SOLIRIS for the treatment of aHUS appear similar in pediatric and adult patients [see Adverse Reactions (6.1), and Clinical Studies (14.2)].

gMG

The safety and effectiveness of SOLIRIS for the treatment of gMG have been established in pediatric patients 6 years of age and older. Use of SOLIRIS in pediatric patients for this indication is supported by evidence from an adequate and well-controlled trial in adults with additional pharmacokinetic and safety data in pediatric patients with gMG who are 12 years of age and older, and pharmacokinetic and safety data in other pediatric populations aged 6 to less than 12 years [see Dosage and Administration (2.4), Adverse Reactions (6.1), Clinical Pharmacology (12.3), and Clinical Studies (14.2)].

Safety and effectiveness of SOLIRIS for the treatment of gMG in pediatric patients below the age of 6 years have not been established.

Vaccinations

Administer vaccinations for the prevention of infection due to Neisseria meningitidis, Streptococcus pneumoniae and Haemophilus influenzae type b (Hib) according to ACIP guidelines [see Warnings and Precautions (5.1, 5.3)].

8.5 Geriatric Use

Fifty-one patients 65 years of age or older (15 with PNH, 4 with aHUS, 26 with gMG, and 6 with NMOSD) were treated with SOLIRIS in clinical trials in the approved indications. Although there were no apparent age-related differences observed in these studies, the number of patients aged 65 and over is not sufficient to determine whether they respond differently from younger patients.

11 DESCRIPTION

Eculizumab, a complement inhibitor, is a recombinant humanized monoclonal IgG2/4κ antibody produced by murine myeloma cell culture and purified by standard bioprocess technology. Eculizumab contains human constant regions from human IgG2 sequences and human IgG4 sequences and murine complementarity-determining regions grafted onto the human framework light- and heavy-chain variable regions. Eculizumab is composed of two 448 amino acid heavy chains and two 214 amino acid light chains and has a molecular weight of approximately 148 kDa.

SOLIRIS (eculizumab) injection is a sterile, clear, colorless, preservative-free 10 mg/mL solution for intravenous infusion and is supplied in 30-mL single-dose vials. The product is formulated at pH 7 and each 30 mL vial contains 300 mg of eculizumab, polysorbate 80 (6.6 mg) (vegetable origin), sodium chloride (263.1 mg), sodium phosphate dibasic (53.4 mg), sodium phosphate monobasic (13.8 mg), and Water for Injection, USP.

12 CLINICAL PHARMACOLOGY

12.1 Mechanism of Action

Eculizumab, the active ingredient in SOLIRIS, is a monoclonal antibody that specifically binds to the complement protein C5 with high affinity, thereby inhibiting its cleavage to C5a and C5b and preventing the generation of the terminal complement complex C5b-9.

SOLIRIS inhibits terminal complement-mediated intravascular hemolysis in PNH patients and complement-mediated thrombotic microangiopathy (TMA) in patients with aHUS.

The precise mechanism by which eculizumab exerts its therapeutic effect in gMG patients is unknown, but is presumed to involve reduction of terminal complement complex C5b-9 deposition at the neuromuscular junction.

The precise mechanism by which eculizumab exerts its therapeutic effect in NMOSD is unknown, but is presumed to involve inhibition of aquaporin-4-antibody induced terminal complement C5b-9 deposition.

12.2 Pharmacodynamics

In the placebo-controlled clinical study (PNH Study 1), SOLIRIS when administered as recommended reduced serum LDH levels from 2200 ± 1034 U/L (mean ± SD) at baseline to 700 ± 388 U/L by week one and maintained the effect through the end of the study at week 26 (327 ± 433 U/L) in patients with PNH. In the single arm clinical study (PNH Study 2), the effect was maintained through week 52 [see Clinical Studies (14)].

In patients with PNH, aHUS, gMG, and NMOSD, free C5 concentrations of < 0.5 mcg/mL was correlated with complete blockade of terminal complement activity.

12.3 Pharmacokinetics

Following intravenous maintenance doses of 900 mg once every 2 weeks in patients with PNH, the week 26 observed mean ± SD serum eculizumab maximum concentration (Cmax) was 194 ± 76 mcg/mL and the trough concentration (Ctrough) was 97 ± 60 mcg/mL. Following intravenous maintenance doses of 1200 mg once every 2 weeks in patients with aHUS, the week 26 observed mean ± SD Ctrough was 242 ± 101 mcg/mL. Following intravenous maintenance doses of 1200 mg once every 2 weeks in adult patients with gMG, the week 26 observed mean ± SD Cmax was 783 ± 288 mcg/mL and the Ctrough was 341 ± 172 mcg/mL. Following intravenous maintenance doses of 1200 mg once every 2 weeks in patients with NMOSD, at week 24, the observed mean±SD Cmax was 877±331 and the Ctrough was 429±188 mcg/mL.

Steady state was achieved 4 weeks after starting eculizumab treatment, with accumulation ratio of approximately 2-fold in all studied indications. Population pharmacokinetic analyses showed that eculizumab pharmacokinetics were dose-linear and time-independent over the 600 mg to 1200 mg dose range, with inter-individual variability of 21% to 38%.

Distribution

The eculizumab volume of distribution for a typical 70 kg patient was 5 L to 8 L.

Elimination

The half life of eculizumab ranged between 141 h and 882 h.

Plasma exchange or infusion increased the clearance of eculizumab by approximately 6.01-fold and reduced the half-life to 90.2 h. Supplemental dosing is recommended when SOLIRIS is administered to patients receiving plasma exchange or infusion [see Dosage and Administration (2.5)].

Specific Populations

Age, Sex, and Race

The pharmacokinetics of eculizumab were not affected by age (2 months to 85 years), sex, or race.

Renal Impairment

Renal function did not affect the pharmacokinetics of eculizumab in PNH (creatinine clearance of 8 mL/min to 396 mL/min calculated using Cockcroft-Gault formula), aHUS (estimated glomerular filtration rate [eGFR] of 5 mL/min/1.73 m^2 to105 mL/min/1.73 m^2 using the Modification of Diet in Renal Disease [MDRD] formula), or gMG patients (eGFR of 44 mL/min/1.73 m^2 to 168 mL/min/1.73 m^2 using MDRD formula).

12.6 Immunogenicity

The observed incidence of anti-drug antibodies is highly dependent on the sensitivity(s) and specificity of the assay. Differences in assay methods preclude meaningful comparisons of the incidence of anti-drug antibodies in the studies described below with the incidence of anti-drug antibodies in other studies, including those of SOLIRIS or of other eculizumab products.

The immunogenicity of SOLIRIS has been evaluated using two different immunoassays for the detection of anti-eculizumab antibodies: a direct enzyme-linked immunosorbent assay (ELISA) using the Fab fragment of eculizumab as target was used for the PNH indication; and an electro-chemiluminescence (ECL) bridging assay using the eculizumab whole molecule as target was used for the aHUS, gMG, and NMOSD indications, as well as for additional patients with PNH.

In the PNH population, antibodies to SOLIRIS were detected in 3/196 (2%) patients using the ELISA assay and in 5/161 (3%) patients using the ECL assay during the entire treatment period. In the aHUS population, antibodies to SOLIRIS were detected in 3/100 (3%) patients using the ECL assay during the entire treatment period. In the gMG population, none of the 62 adult patients and 11 pediatric patients had antibodies to SOLIRIS detected following the 26-week active treatment. In the NMOSD population, antibodies to SOLIRIS were detected in 2/96 (2%) patients during the entire treatment period.

An ECL based neutralizing assay with a low sensitivity of 2 mcg/mL was performed to detect neutralizing antibodies for the 5 patients with PNH, the 3 patients with aHUS, and the 2 patients with NMOSD with anti-eculizumab antibody positive samples using the ECL assay. Two of 161 patients with PNH (1.2%) and 1 of 100 patients with aHUS (1%), and none of the 96 patients with NMOSD had low positive values for neutralizing antibodies.

No apparent correlation of antibody development to clinical response was observed.

13 NONCLINICAL TOXICOLOGY

13.1 Carcinogenesis, Mutagenesis, Impairment of Fertility

Long-term animal carcinogenicity studies of eculizumab have not been conducted.

Genotoxicity studies have not been conducted with eculizumab.

Effects of eculizumab upon fertility have not been studied in animals. Intravenous injections of male and female mice with a murine anti-C5 antibody at up to 4-8 times the equivalent of the clinical dose of SOLIRIS had no adverse effects on mating or fertility.

14 CLINICAL STUDIES

14.1 Paroxysmal Nocturnal Hemoglobinuria (PNH)

The safety and efficacy of SOLIRIS in PNH patients with hemolysis were assessed in a randomized, double-blind, placebo-controlled 26 week study (PNH Study 1, NCT00122330); PNH patients were also treated with SOLIRIS in a single arm 52 week study (PNH Study 2, NCT00122304) and in a long-term extension study (E05-001, NCT00122317). Patients received meningococcal vaccination prior to receipt of SOLIRIS. In all studies, the dose of SOLIRIS was 600 mg study drug every 7 ± 2 days for 4 weeks, followed by 900 mg 7 ± 2 days later, then 900 mg every 14 ± 2 days for the study duration. SOLIRIS was administered as an intravenous infusion over 25 - 45 minutes.

PNH Study 1

PNH patients with at least four transfusions in the prior 12 months, flow cytometric confirmation of at least 10% PNH cells and platelet counts of at least 100,000/microliter were randomized to either SOLIRIS (n = 43) or placebo (n = 44). Prior to randomization, all patients underwent an initial observation period to confirm the need for RBC transfusion and to identify the hemoglobin concentration (the "set-point") which would define each patient's hemoglobin stabilization and transfusion outcomes. The hemoglobin set-point was less than or equal to 9 g/dL in patients with symptoms and was less than or equal to 7 g/dL in patients without symptoms. Endpoints related to hemolysis included the numbers of patients achieving hemoglobin stabilization, the number of RBC units transfused, fatigue, and health-related quality of life. To achieve a designation of hemoglobin stabilization, a patient had to maintain a hemoglobin concentration above the hemoglobin set-point and avoid any RBC transfusion for the entire 26 week period. Hemolysis was monitored mainly by the measurement of serum LDH levels, and the proportion of PNH RBCs was monitored by flow cytometry. Patients receiving anticoagulants and systemic corticosteroids at baseline continued these medications.

Major baseline characteristics were balanced (see Table 11).

Table 11: PNH Study 1 Patient Baseline Characteristics
 | Study 1
Parameter | Placebo (N=44) | SOLIRIS (N=43)
Mean age (SD) | 38 (13) | 42 (16)
Gender - female (%) | 29 (66) | 23 (54)
History of aplastic anemia or myelodysplastic syndrome (%) | 12 (27) | 8 (19)
Patients with history of thrombosis (events) | 8 (11) | 9 (16)
Concomitant anticoagulants (%) | 20 (46) | 24 (56)
Concomitant steroids/immunosuppressant treatments (%) | 16 (36) | 14 (33)
Packed RBC units transfused per patient in previous 12 months (median (Q1,Q3)) | 17 (14, 25) | 18 (12, 24)
Mean Hgb level (g/dL) at setpoint (SD) | 8 (1) | 8 (1)
Pre-treatment LDH levels (median, U/L) | 2,234 | 2,032
Free hemoglobin at baseline (median, mg/dL) | 46 | 41

Patients treated with SOLIRIS had significantly reduced (p< 0.001) hemolysis resulting in improvements in anemia as indicated by increased hemoglobin stabilization and reduced need for RBC transfusions compared to placebo treated patients (see Table 12). These effects were seen among patients within each of the three pre-study RBC transfusion strata (4 - 14 units; 15 - 25 units; > 25 units). After 3 weeks of SOLIRIS treatment, patients reported less fatigue and improved health-related quality of life. Because of the study sample size and duration, the effects of SOLIRIS on thrombotic events could not be determined.

Table 12: PNH Study 1 Results
 | Placebo (N=44) | SOLIRIS (N=43)
Percentage of patients with stabilized hemoglobin levels | 0 | 49
Packed RBC units transfused per patient (median) | 10 | 0
(range) | (2 - 21) | (0 - 16)
Transfusion avoidance (%) | 0 | 51
LDH levels at end of study (median, U/L) | 2,167 | 239
Free hemoglobin at end of study (median, mg/dL) | 62 | 5

PNH Study 2 and Extension Study

PNH patients with at least one transfusion in the prior 24 months and at least 30,000 platelets/microliter received SOLIRIS over a 52-week period. Concomitant medications included anti-thrombotic agents in 63% of the patients and systemic corticosteroids in 40% of the patients. Overall, 96 of the 97 enrolled patients completed the study (one patient died following a thrombotic event). A reduction in intravascular hemolysis as measured by serum LDH levels was sustained for the treatment period and resulted in a reduced need for RBC transfusion and less fatigue. 187 SOLIRIS-treated PNH patients were enrolled in a long term extension study. All patients sustained a reduction in intravascular hemolysis over a total SOLIRIS exposure time ranging from 10 to 54 months. There were fewer thrombotic events with SOLIRIS treatment than during the same period of time prior to treatment. However, the majority of patients received concomitant anticoagulants; the effects of anticoagulant withdrawal during SOLIRIS therapy was not studied [see Warnings and Precautions (5.5)].

14.2 Atypical Hemolytic Uremic Syndrome (aHUS)

Five single-arm studies [four prospective: C08-002A/B (NCT00844545 and NCT00844844), C08-003A/B (NCT00838513 and NCT00844428), C10-003 (NCT01193348), and C10-004 (NCT01194973); and one retrospective: C09-001r (NCT01770951)] evaluated the safety and efficacy of SOLIRIS for the treatment of aHUS. Patients with aHUS received meningococcal vaccination prior to receipt of SOLIRIS or received prophylactic treatment with antibiotics until 2 weeks after vaccination. In all studies, the dose of SOLIRIS in adult and adolescent patients was 900 mg every 7 ± 2 days for 4 weeks, followed by 1200 mg 7 ± 2 days later, then 1200 mg every 14 ± 2 days thereafter. The dosage regimen for pediatric patients weighing less than 40 kg enrolled in Study C09-001r and Study C10-003 was based on body weight [see Dosage and Administration (2.3)]. Efficacy evaluations were based on thrombotic microangiopathy (TMA) endpoints.

Endpoints related to TMA included the following:

- platelet count change from baseline
- hematologic normalization (maintenance of normal platelet counts and LDH levels for at least four weeks)
- complete TMA response (hematologic normalization plus at least a 25% reduction in serum creatinine for a minimum of four weeks)
- TMA-event free status (absence for at least 12 weeks of a decrease in platelet count of >25% from baseline, plasma exchange or plasma infusion, and new dialysis requirement)
- Daily TMA intervention rate (defined as the number of plasma exchange or plasma infusion interventions and the number of new dialyses required per patient per day).

aHUS Resistant to PE/PI (Study C08-002A/B)

Study C08-002A/B enrolled patients who displayed signs of thrombotic microangiopathy (TMA) despite receiving at least four PE/PI treatments the week prior to screening. One patient had no PE/PI the week prior to screening because of PE/PI intolerance. In order to qualify for enrollment, patients were required to have a platelet count ≤150 × 10^9/L, evidence of hemolysis such as an elevation in serum LDH, and serum creatinine above the upper limits of normal, without the need for chronic dialysis. The median patient age was 28 (range: 17 to 68 years). Patients enrolled in Study C08-002A/B were required to have ADAMTS13 activity level above 5%; observed range of values in the trial were 70%-121%. Seventy-six percent of patients had an identified complement regulatory factor mutation or auto-antibody. Table 13 summarizes the key baseline clinical and disease-related characteristics of patients enrolled in Study C08-002A/B.

Table 13: Baseline Characteristics of Patients Enrolled in Study C08-002A/B
Parameter | C08-002A/B (N=17)
Time from aHUS diagnosis until screening in months, median (min, max) | 10 (0.26, 236)
Time from current clinical TMA manifestation until screening in months, median (min, max) | <1 (<1, 4)
Baseline platelet count (× 10^9/L), median (range) | 118 (62, 161)
Baseline LDH (U/L), median (range) | 269 (134, 634)

Patients in Study C08-002A/B received SOLIRIS for a minimum of 26 weeks. In Study C08-002A/B, the median duration of SOLIRIS therapy was approximately 100 weeks (range: 2 weeks to 145 weeks).

Renal function, as measured by eGFR, was improved and maintained during SOLIRIS therapy. The mean eGFR (± SD) increased from 23 ± 15 mL/min/1.73m^2 at baseline to 56 ± 40 mL/min/1.73m^2 by 26 weeks; this effect was maintained through 2 years (56 ± 30 mL/min/1.73m^2). Four of the five patients who required dialysis at baseline were able to discontinue dialysis.

Reduction in terminal complement activity and an increase in platelet count relative to baseline were observed after commencement of SOLIRIS. SOLIRIS reduced signs of complement-mediated TMA activity, as shown by an increase in mean platelet counts from baseline to 26 weeks. In Study C08-002A/B, mean platelet count (± SD) increased from 109 ± 32 ×10^9/L at baseline to 169 ± 72 ×10^9/L by one week; this effect was maintained through 26 weeks (210 ± 68 ×10^9/L), and 2 years (205 ± 46 ×10^9/L). When treatment was continued for more than 26 weeks, two additional patients achieved Hematologic Normalization as well as Complete TMA response. Hematologic Normalization and Complete TMA response were maintained by all responders. In Study C08-002A/B, responses to SOLIRIS were similar in patients with and without identified mutations in genes encoding complement regulatory factor proteins.

Table 14 summarizes the efficacy results for Study C08-002A/B.

Table 14: Efficacy Results for Study C08-002A/B
Efficacy Parameter | Study C08-002A/B at 26 wks [At data cut-off (September 8, 2010).] (N=17) | Study C08-002A/B at 2 yrs [At data cut-off (April 20, 2012).] (N=17)
Complete TMA response, n (%) | 11 (65) | 13 (77)
Median Duration of complete TMA response, weeks (range) | 38 (25, 56) | 99 (25, 139)
eGFR improvement ≥15 mL/min/1.73 m^2, n (%) | 9 (53) | 10 (59)
Median duration of eGFR improvement, days (range) | 251 (70, 392) | ND
Hematologic normalization, n (%) Median Duration of hematologic normalization, weeks (range) | 13 (76) 37 (25, 62) | 15 (88) 99 (25, 145)
TMA event-free status, n (%) | 15 (88) | 15 (88)
Daily TMA intervention rate, median (range)
Before eculizumab | 0.82 (0.04, 1.52) | 0.82 (0.04, 1.52)
On eculizumab treatment | 0 (0, 0.31) | 0 (0, 0.36)

aHUS Sensitive to PE/PI (Study C08-003A/B)

Study C08-003A/B enrolled patients undergoing chronic PE/PI who generally did not display hematologic signs of ongoing thrombotic microangiopathy (TMA). All patients had received PT at least once every two weeks, but no more than three times per week, for a minimum of eight weeks prior to the first SOLIRIS dose. Patients on chronic dialysis were permitted to enroll in Study C08-003A/B. The median patient age was 28 years (range: 13 to 63 years). Patients enrolled in Study C08-003A/B were required to have ADAMTS13 activity level above 5%; observed range of values in the trial were 37%-118%. Seventy percent of patients had an identified complement regulatory factor mutation or auto-antibody. Table 15 summarizes the key baseline clinical and disease-related characteristics of patients enrolled in Study C08-003A/B.

Table 15: Baseline Characteristics of Patients Enrolled in Study C08-003A/B
Parameter | Study C08-003A/B (N=20)
Time from aHUS diagnosis until screening in months, median (min, max) | 48 (0.66, 286)
Time from current clinical TMA manifestation until screening in months, median (min, max) | 9 (1, 45)
Baseline platelet count (× 10^9/L), median (range) | 218 (105, 421)
Baseline LDH (U/L), median (range) | 200 (151, 391)

Patients in Study C08-003A/B received SOLIRIS for a minimum of 26 weeks. In Study C08-003A/B, the median duration of SOLIRIS therapy was approximately 114 weeks (range: 26 to 129 weeks).

Renal function, as measured by eGFR, was maintained during SOLIRIS therapy. The mean eGFR (± SD) was 31 ± 19 mL/min/1.73m^2 at baseline, and was maintained through 26 weeks (37 ± 21 mL/min/1.73m^2) and 2 years (40 ± 18 mL/min/1.73m^2). No patient required new dialysis with SOLIRIS.

Reduction in terminal complement activity was observed in all patients after the commencement of SOLIRIS. SOLIRIS reduced signs of complement-mediated TMA activity, as shown by an increase in mean platelet counts from baseline to 26 weeks. Platelet counts were maintained at normal levels despite the elimination of PE/PI. The mean platelet count (± SD) was 228 ± 78 × 10^9/L at baseline, 233 ± 69 × 10^9/L at week 26, and 224 ± 52 × 10^9/L at 2 years. When treatment was continued for more than 26 weeks, six additional patients achieved Complete TMA response. Complete TMA Response and Hematologic Normalization were maintained by all responders. In Study C08-003A/B, responses to SOLIRIS were similar in patients with and without identified mutations in genes encoding complement regulatory factor proteins.

Table 16 summarizes the efficacy results for Study C08-003A/B.

Table 16: Efficacy Results for Study C08-003A/B
Efficacy Parameter | Study C08-003A/B at 26 wks [At data cut-off (September 8, 2010).] (N=20) | Study C08-003A/B at 2 yrs [At data cut-off (April 20, 2012).] (N=20)
Complete TMA response, n (%) | 5 (25) | 11 (55)
Median duration of complete TMA response, weeks (range) | 32 (12, 38) | 68 (38, 109)
eGFR improvement ≥15 mL/min/1.73 m^2, n (%) | 1 (5) | 8 (40)
TMA Event-free status n (%) | 16 (80) | 19 (95)
Daily TMA intervention rate, median (range)
Before eculizumab | 0.23 (0.05, 1.07) | 0.23 (0.05, 1.07)
On eculizumab treatment | 0 | 0 (0, 0.01)
Hematologic normalization [In Study C08-003A/B, 85% of patients had normal platelet counts and 80% of patients had normal serum LDH levels at baseline, so hematologic normalization in this population reflects maintenance of normal parameters in the absence of PE/PI.] , n (%) Median duration of hematologic normalization, weeks (range) [Calculated at each post-dose day of measurement (excluding Days 1 to 4) using a repeated measurement ANOVA model.] | 18 (90) 38 (22, 52) | 18 (90) 114 (33, 125)

Retrospective Study in Patients with aHUS (C09-001r)

The efficacy results for the aHUS retrospective study (Study C09-001r) were generally consistent with results of the two prospective studies. SOLIRIS reduced signs of complement-mediated TMA activity, as shown by an increase in mean platelet counts from baseline. Mean platelet count (± SD) increased from 171 ± 83 ×10^9/L at baseline to 233 ±109 ×10^9/L after one week of therapy; this effect was maintained through 26 weeks (mean platelet count (± SD) at week 26: 254 ± 79 ×10^9/L).

A total of 19 pediatric patients (ages 2 months to 17 years) received SOLIRIS in Study C09-001r. The median duration of SOLIRIS therapy was 16 weeks (range 4 to 70 weeks) for children <2 years of age (n=5), 31 weeks (range 19 to 63 weeks) for children 2 to <12 years of age (n=10), and 38 weeks (range 1 to 69 weeks) for patients 12 to <18 years of age (n=4). Fifty-three percent of pediatric patients had an identified complement regulatory factor mutation or auto-antibody.

Overall, the efficacy results for these pediatric patients appeared consistent with what was observed in patients enrolled in Studies C08-002A/B and C08-003A/B (Table 17). No pediatric patient required new dialysis during treatment with SOLIRIS.

Table 17: Efficacy Results in Pediatric Patients Enrolled in Study C09-001r
Efficacy Parameter | <2 yrs (N=5) | 2 to <12 yrs (N=10) | 12 to <18 yrs (N=4) | Total (N=19)
Complete TMA response, n (%) | 2 (40) | 5 (50) | 1 (25) | 8 (42)
Patients with eGFR improvement ≥ 15 mL/min/1.73 m^2, n (%) [Of the 9 patients who experienced an eGFR improvement of at least 15 mL/min/1.73 m^2, one received dialysis throughout the study period and another received SOLIRIS as prophylaxis following renal allograft transplantation.] | 2 (40) | 6 (60) | 1 (25) | 9 (47)
Platelet count normalization, n (%) [Platelet count normalization was defined as a platelet count of at least 150,000 × 10^9/L on at least two consecutive measurements spanning a period of at least 4 weeks.] | 4 (80) | 10 (100) | 3 (75) | 17 (89)
Hematologic Normalization, n (%) | 2 (40) | 5 (50) | 1 (25) | 8 (42)
Daily TMA intervention rate, median (range)
Before eculizumab | 1 (0, 2) | <1 (0.07, 1.46) | <1 (0, 1) | 0.31 (0.00, 2.38)
On eculizumab treatment | <1 (0, <1) | 0 (0, <1) | 0 (0, <1) | 0.00 (0.00, 0.08)

Adult Patients with aHUS (Study C10-004)

Study C10-004 enrolled patients who displayed signs of thrombotic microangiopathy (TMA). In order to qualify for enrollment, patients were required to have a platelet count < lower limit of normal range (LLN), evidence of hemolysis such as an elevation in serum LDH, and serum creatinine above the upper limits of normal, without the need for chronic dialysis. The median patient age was 35 (range: 18 to 80 years). All patients enrolled in Study C10-004 were required to have ADAMTS13 activity level above 5%; observed range of values in the trial were 28%-116%. Fifty-one percent of patients had an identified complement regulatory factor mutation or auto-antibody. A total of 35 patients received PE/PI prior to eculizumab. Table 18 summarizes the key baseline clinical and disease-related characteristics of patients enrolled in Study C10-004.

Table 18: Baseline Characteristics of Patients Enrolled in Study C10-004
Parameter | Study C10-004 (N=41)
Time from aHUS diagnosis until start of study drug in months, median (range) | 0.79 (0.03 – 311)
Time from current clinical TMA manifestation until first study dose in months, median (range) | 0.52 (0.03-19)
Baseline platelet count (× 10^9/L), median (range) | 125 (16 – 332)
Baseline LDH (U/L), median (range) | 375 (131 – 3318)

Patients in Study C10-004 received SOLIRIS for a minimum of 26 weeks. In Study C10-004, the median duration of SOLIRIS therapy was approximately 50 weeks (range: 13 weeks to 86 weeks).

Renal function, as measured by eGFR, was improved during SOLIRIS therapy. The mean eGFR (± SD) increased from 17 ± 12 mL/min/1.73m^2 at baseline to 47 ± 24 mL/min/1.73m^2 by 26 weeks. Twenty of the 24 patients who required dialysis at study baseline were able to discontinue dialysis during SOLIRIS treatment.

Reduction in terminal complement activity and an increase in platelet count relative to baseline were observed after commencement of SOLIRIS. SOLIRIS reduced signs of complement-mediated TMA activity, as shown by an increase in mean platelet counts from baseline to 26 weeks. In Study C10-004, mean platelet count (± SD) increased from 119 ± 66 ×10^9/L at baseline to 200 ± 84 ×10^9/L by one week; this effect was maintained through 26 weeks (mean platelet count (± SD) at week 26: 252 ± 70 ×10^9/L). In Study C10-004, responses to SOLIRIS were similar in patients with and without identified mutations in genes encoding complement regulatory factor proteins or auto-antibodies to factor H.

Table 19 summarizes the efficacy results for Study C10-004.

Table 19: Efficacy Results for Study C10-004
Efficacy Parameter | Study C10-004 (N=41)
Complete TMA response, n (%), | 23 (56)
95% CI | 40,72
Median duration of complete TMA response, weeks (range) | 42 (6, 75)
Patients with eGFR improvement ≥ 15 mL/min/1.73m^2, n (%) | 22 (54)
Hematologic Normalization, n (%) | 36 (88)
Median duration of hematologic normalization, weeks (range) | 46 (10, 75)
TMA Event-free Status, n (%) | 37 (90)
Daily TMA Intervention Rate, median (range)
Before eculizumab | 0.63 (0, 1.38)
On eculizumab treatment | 0 (0, 0.58)

Pediatric and Adolescent Patients with aHUS (Study C10-003)

Study C10-003 enrolled patients who were required to have a platelet count < lower limit of normal range (LLN), evidence of hemolysis such as an elevation in serum LDH above the upper limits of normal, serum creatinine level ≥97 percentile for age without the need for chronic dialysis. The median patient age was 6.5 (range: 5 months to 17 years). Patients enrolled in Study C10-003 were required to have ADAMTS13 activity level above 5%; observed range of values in the trial were 38%-121%. Fifty percent of patients had an identified complement regulatory factor mutation or auto-antibody. A total of 10 patients received PE/PI prior to eculizumab. Table 20 summarizes the key baseline clinical and disease-related characteristics of patients enrolled in Study C10-003.

Table 20: Baseline Characteristics of Patients Enrolled in Study C10-003
Parameter | Patients 1 month to <12 years (N=18) | All Patients (N=22)
Time from aHUS diagnosis until start of study drug in months, median (range) | 0.51 (0.03 – 58) | 0.56 (0.03-191)
Time from current clinical TMA manifestation until first study dose in months, median (range) | 0.23 (0.03 – 4) | 0.2 (0.03-4)
Baseline platelet count (× 10^9/L), median (range) | 110 (19-146) | 91 (19-146)
Baseline LDH (U/L) median (range) | 1510 (282-7164) | 1244 (282-7164)

Patients in Study C10-003 received SOLIRIS for a minimum of 26 weeks. In Study C10-003, the median duration of SOLIRIS therapy was approximately 44 weeks (range: 1 dose to 88 weeks).

Renal function, as measured by eGFR, was improved during SOLIRIS therapy. The mean eGFR (± SD) increased from 33 ± 30 mL/min/1.73m^2 at baseline to 98 ± 44 mL/min/1.73m^2 by 26 weeks. Among the 20 patients with a CKD stage ≥2 at baseline, 17 (85%) achieved a CKD improvement of ≥1 stage. Among the 16 patients ages 1 month to <12 years with a CKD stage ≥2 at baseline, 14 (88%) achieved a CKD improvement by ≥1 stage. Nine of the 11 patients who required dialysis at study baseline were able to discontinue dialysis during SOLIRIS treatment. Responses were observed across all ages from 5 months to 17 years of age.

Reduction in terminal complement activity was observed in all patients after commencement of SOLIRIS. SOLIRIS reduced signs of complement-mediated TMA activity, as shown by an increase in mean platelet counts from baseline to 26 weeks. The mean platelet count (± SD) increased from 88 ± 42 ×10^9/L at baseline to 281 ± 123 ×10^9/L by one week; this effect was maintained through 26 weeks (mean platelet count (±SD) at week 26: 293 ± 106 ×10^9/L). In Study C10-003, responses to SOLIRIS were similar in patients with and without identified mutations in genes encoding complement regulatory factor proteins or auto-antibodies to factor H.

Table 21 summarizes the efficacy results for Study C10-003.

Table 21: Efficacy Results for Study C10-003
Efficacy Parameter | Patients 1 month to <12 years (N=18) | All Patients (N=22)
Complete TMA response, n (%) 95% CI Median Duration of complete TMA response, weeks (range) [Through data cutoff (October 12, 2012).] | 11 (61) 36, 83 40 (14, 77) | 14 (64) 41, 83 37 (14, 77)
eGFR improvement ≥15 mL/min/ 1.73∙m^2∙n (%) | 16 (89) | 19 (86)
Complete Hematologic Normalization, n (%) Median Duration of complete hematologic normalization, weeks (range) | 14 (78) 38 (14, 77) | 18 (82) 38 (14, 77)
TMA Event-Free Status, n (%) | 17 (94) | 21 (95)
Daily TMA Intervention rate, median (range) Before eculizumab treatment On eculizumab treatment | 0.2 (0, 1.7) 0 (0, 0.01) | 0.4 (0, 1.7) 0 (0, 0.01)

14.3 Generalized Myasthenia Gravis (gMG)

The efficacy of SOLIRIS for the treatment of gMG was established in Study ECU-MG-301 (NCT01997229), a 26-week randomized, double-blind, parallel-group, placebo-controlled, multi-center trial that enrolled adult patients who met the following criteria at screening:

1. Positive serologic test for anti-AChR antibodies,
2. Myasthenia Gravis Foundation of America (MGFA) Clinical Classification Class II to IV,
3. MG-Activities of Daily Living (MG-ADL) total score ≥6,
4. Failed treatment over 1 year or more with 2 or more immunosuppressive therapies (ISTs) either in combination or as monotherapy, or failed at least 1 IST and required chronic plasmapheresis or plasma exchange (PE) or intravenous immunoglobulin (IVIg).

A total of 62 patients were randomized to receive SOLIRIS treatment and 63 were randomized to receive placebo. Baseline characteristics were similar between treatment groups, including age at diagnosis (38 years in each group), gender [66% female (eculizumab) versus 65% female (placebo)], and duration of gMG [9.9 (eculizumab) versus 9.2 (placebo) years]. Over 95% of patients in each group were receiving acetylcholinesterase (AchE) inhibitors, and 98% were receiving immunosuppressant therapies (ISTs). Approximately 50% of each group had been previously treated with at least 3 ISTs.

SOLIRIS was administered according to the recommended dosage regimen [see Dosage and Administration (2.4)].

The primary efficacy endpoint for Study ECU-MG-301 was a comparison of the change from baseline between treatment groups in the Myasthenia Gravis-Specific Activities of Daily Living scale (MG-ADL) total score at Week 26. The MG-ADL is a categorical scale that assesses the impact on daily function of 8 signs or symptoms that are typically affected in gMG. Each item is assessed on a 4-point scale where a score of 0 represents normal function and a score of 3 represents loss of ability to perform that function (total score 0-24). A statistically significant difference favoring SOLIRIS was observed in the mean change from baseline to Week 26 in MG-ADL total scores [-4.2 points in the SOLIRIS-treated group compared with -2.3 points in the placebo-treated group (p=0.006)].

A key secondary endpoint in Study ECU-MG-301 was the change from baseline in the Quantitative Myasthenia Gravis (QMG) total score at Week 26. The QMG is a 13-item categorical scale assessing muscle weakness. Each item is assessed on a 4-point scale where a score of 0 represents no weakness and a score of 3 represents severe weakness (total score 0-39). A statistically significant difference favoring SOLIRIS was observed in the mean change from baseline to Week 26 in QMG total scores [-4.6 points in the SOLIRIS-treated group compared with -1.6 points in the placebo-treated group (p=0.001)].

The results of the analysis of the MG-ADL and QMG from Study ECU-MG-301 are shown in Table 22.

Table 22: Analysis of Change from Baseline to Week 26 in MG-ADL and QMG Total Scores in Study ECU-MG-301
Efficacy Endpoints | SOLIRIS-LS Mean (N=62) (SEM) | Placebo-LS Mean (N=63) (SEM) | SOLIRIS change relative to placebo – LS Mean Difference (95% CI) | p-values
MG-ADL | -4.2 (0.49) | -2.3 (0.48) | -1.9 (-3.3, -0.6) | (0.006 [in least square means at Week 26 using a repeated measure analysis;] ; 0.014 [in ranks at Week 26 using a worst rank analysis).])
QMG | -4.6 (0.60) | -1.6 (0.59) | -3.0 (-4.6, -1.3) | (0.001 ; 0.005)
SEM= Standard Error of the Mean;
SOLIRIS-LSMean = least square mean for the treatment group;
Placebo-LSMean = least square mean for the placebo group;
LSMean-Difference (95% CI) = Difference in least square mean with 95% confidence interval;
p-values (testing the null hypothesis that there is no difference between the two treatment arms

In Study ECU-MG-301, a clinical response was defined in the MG-ADL total score as at least a 3-point improvement and in QMG total score as at least a 5-point improvement. The proportion of clinical responders at Week 26 with no rescue therapy was statistically significantly higher for SOLIRIS compared to placebo for both measures. For both endpoints, and also at higher response thresholds (≥4-, 5-, 6-, 7-, or 8-point improvement on MG-ADL, and ≥6-, 7-, 8-, 9-, or 10-point improvement on QMG), the proportion of clinical responders was consistently greater for SOLIRIS compared to placebo. Available data suggest that clinical response is usually achieved by 12 weeks of SOLIRIS treatment.

14.4 Neuromyelitis Optica Spectrum Disorder (NMOSD)

The efficacy of SOLIRIS for the treatment of NMOSD was established in NMOSD Study 1 (NCT01892345), a randomized, double-blind, placebo-controlled trial that enrolled 143 patients with NMOSD who were anti-AQP4 antibody positive and met the following criteria at screening:

1. History of at least 2 relapses in last 12 months or 3 relapses in the last 24 months, with at least 1 relapse in the 12 months prior to screening,
2. Expanded Disability Status Scale (EDSS) score ≤ 7 (consistent with the presence of at least limited ambulation with aid),
3. If on immunosuppressive therapy (IST), on a stable dose regimen,
4. The use of concurrent corticosteroids was limited to 20 mg per day or less,
5. Patients were excluded if they had been treated with rituximab or mitoxantrone within 3 months or with IVIg within 3 weeks prior to screening.

A total of 96 patients were randomized to receive SOLIRIS treatment and 47 were randomized to receive placebo.

The baseline demographic and disease characteristics were balanced between treatment groups. During the treatment phase of the trial, 76% percent of patients received concomitant IST, including chronic corticosteroids; 24% of patients did not receive concomitant IST or chronic corticosteroids during the treatment phase of the trial.

SOLIRIS was administered according to the recommended dosage regimen [see Dosage and Administration (2.4)].

The primary endpoint for NMOSD Study 1 was the time to the first adjudicated on-trial relapse. The time to the first adjudicated on-trial relapse was significantly longer in SOLIRIS-treated patients compared to placebo-treated patients (relative risk reduction 94%; hazard ratio 0.058; p < 0.0001) (Figure 1).

Figure 1: Kaplan-Meier Survival Estimates for Time to First Adjudicated On-Trial Relapse – Full Analysis Set

Note: Patients who did not experience an adjudicated on-trial relapse were censored at the end of the study period. Abbreviations: CI = confidence interval

SOLIRIS-treated patients experienced similar improvement in time to first adjudicated on-trial relapse with or without concomitant treatment. SOLIRIS-treated patients had a 96% relative reduction in the adjudicated on-trial annualized relapse rate (ARR) compared to patients on placebo, as shown in Table 23.

Table 23: Adjudicated On-trial Annualized Relapse Rate – Full Analysis Set
Variable | Statistic | Placebo (N=47) | SOLIRIS (N=96)
Total number of relapses | Sum | 21 | 3
Adjusted adjudicated ARR [Based on a Poisson regression adjusted for randomization strata and historical ARR in 24 months prior to screening.] | Rate | 0.350 | 0.016
Treatment effect | Rate ratio (eculizumab/placebo) | … | 0.045
Treatment effect | p-value | … | <0.0001
ARR = annualized relapse rate

Compared to placebo-treated patients, SOLIRIS-treated patients had reduced annualized rates of hospitalizations (0.04 for SOLIRIS versus 0.31 for placebo), of corticosteroid administrations to treat acute relapses (0.07 for SOLIRIS versus 0.42 for placebo), and of plasma exchange treatments (0.02 for SOLIRIS versus 0.19 for placebo).

16 HOW SUPPLIED/STORAGE AND HANDLING

SOLIRIS (eculizumab) injection is a sterile, preservative-free, clear, colorless solution supplied as one 300 mg/30 mL (10 mg/mL) single-dose vial per carton (NDC 25682-001-01).

STORAGE AND HANDLING

Store SOLIRIS vials refrigerated at 2°-8° C (36°-46° F) in the original carton to protect from light until time of use. SOLIRIS vials may be stored in the original carton at controlled room temperature (not more than 25° C/77° F) for only a single period up to 3 days. Do not use beyond the expiration date stamped on the carton. Refer to Dosage and Administration (2) for information on the stability and storage of diluted solutions of SOLIRIS.

DO NOT FREEZE. DO NOT SHAKE.

17 PATIENT COUNSELING INFORMATION

Advise the patients and/or caregivers to read the FDA-approved patient labeling (Medication Guide).

Serious Meningococcal Infections

Advise patients of the risk of serious meningococcal infection. Inform patients of the need to complete or update their meningococcal vaccinations at least 2 weeks prior to receiving the first dose of SOLIRIS or receive antibacterial drug prophylaxis if SOLIRIS treatment must be initiated immediately and they have not been previously vaccinated. Inform patients of the requirement to be revaccinated according to current ACIP recommendations for meningococcal infection while on SOLIRIS therapy [see Warnings and Precautions (5.1)].

Inform patients that vaccination may not prevent serious meningococcal infection and to seek immediate medical attention if the following signs or symptoms occur [see Warnings and Precautions (5.1)]:

- fever
- fever and a rash
- fever with high heart rate
- headache with nausea or vomiting
- headache and a fever
- headache with a stiff neck or stiff back
- confusion
- muscle aches with flu-like symptoms
- eyes sensitive to light

Inform patients that they will be given a Patient Safety Card for SOLIRIS that they should carry with them at all times during and for 3 months following treatment with SOLIRIS. This card describes symptoms which, if experienced, should prompt the patient to immediately seek medical evaluation.

ULTOMIRIS and SOLIRIS REMS

SOLIRIS is available only through a restricted program called ULTOMIRIS and SOLIRIS REMS [see Warnings and Precautions (5.2)].

Inform the patient of the following notable requirements:

- Patients must receive counseling about the risk of serious meningococcal infections.
- Patients must receive written educational materials about this risk.
- Patients must be instructed to carry the Patient Safety Card with them at all times during and for 3 months following treatment with SOLIRIS.
- Patients must be instructed to complete or update meningococcal vaccines for serogroups A, C, W, Y and B per ACIP recommendations as directed by the prescriber prior to treatment with SOLIRIS.
- Patients must receive antibiotics as directed by the prescriber if they are not up to date with meningococcal vaccines and have to start SOLIRIS right away.

Other Infections

Counsel patients about gonorrhea prevention and advise regular testing for patients at-risk.

Inform patients that there may be an increased risk of other types of infections, particularly those due to encapsulated bacteria.

Aspergillus infections have occurred in immunocompromised and neutropenic patients.

Inform parents or caregivers of children receiving SOLIRIS that their child should be vaccinated against Streptococcus pneumoniae and Haemophilus influenzae type b (Hib) according to current medical guidelines.

Infusion-Related Reactions

Advise patients that administration of SOLIRIS may result in infusion-related reactions.

Discontinuation

Inform patients with PNH that they may develop serious hemolysis due to PNH when SOLIRIS is discontinued and that they will be monitored by their healthcare professional for at least 8 weeks following SOLIRIS discontinuation.

Inform patients with aHUS that there is a potential for TMA complications due to aHUS when SOLIRIS is discontinued and that they will be monitored by their healthcare professional for at least 12 weeks following SOLIRIS discontinuation. Inform patients who discontinue SOLIRIS to keep the Patient Safety Card with them for three months after the last SOLIRIS dose, because the increased risk of meningococcal infection persists for several weeks following discontinuation of SOLIRIS.

Manufactured by:

Alexion Pharmaceuticals, Inc.
121 Seaport Boulevard
Boston, MA 02210 USA

US License Number 1743

This product, or its use, may be covered by one or more US patents, including US Patent No. 6,355,245, US Patent No. 9,732,149 and US Patent No.9,718,880 in addition to others including patents pending.

SOLIRIS is a registered trademark of Alexion Pharmaceuticals, Inc.

© 2025 Alexion Pharmaceuticals, Inc.

MEDICATION GUIDE
SOLIRIS® (so-leer-is)
(eculizumab)
injection, for intravenous use

What is the most important information I should know about SOLIRIS?
SOLIRIS is a medicine that affects your immune system. SOLIRIS may lower the ability of your immune system to fight infections.

- SOLIRIS increases your chance of getting serious meningococcal infections caused by Neisseria meningitidis bacteria. Meningococcal infections may quickly become life-threatening or cause death if not recognized and treated early.
  - You must complete or update your meningococcal vaccine(s) at least 2 weeks before your first dose of SOLIRIS.
  - If you have not completed your meningococcal vaccines and SOLIRIS must be started right away, you should receive the required vaccine(s) as soon as possible.
  - If you have not been vaccinated and SOLIRIS must be started right away, you should also receive antibiotics to take for as long as your healthcare provider tells you.
  - If you had a meningococcal vaccine in the past, you might need additional vaccines before starting SOLIRIS. Your healthcare provider will decide if you need additional meningococcal vaccines.
  - Meningococcal vaccines do not prevent all meningococcal infections. Call your healthcare provider or get emergency medical care right away if you get any of these signs and symptoms of a serious meningococcal infection:

- fever
- fever with high heart rate
- headache and fever
- confusion
- muscle aches with flu-like symptoms

- fever and a rash
- headache with nausea or vomiting
- headache with a stiff neck or stiff back
- eyes sensitive to light

Your healthcare provider will give you a Patient Safety Card about the risk of serious meningococcal infection. Carry it with you at all times during treatment and for 3 months after your last dose of SOLIRIS. Your risk of meningococcal infection may continue for several weeks after your last dose of SOLIRIS. It is important to show this card to any healthcare provider who treats you. This will help them diagnose and treat you quickly.
SOLIRIS is only available through a program called the ULTOMIRIS and SOLIRIS Risk Evaluation and Mitigation Strategy (REMS).
Before you can receive SOLIRIS, your healthcare provider must:

- enroll in the ULTOMIRIS and SOLIRIS REMS program
- counsel you about the risk of serious meningococcal infections
- give you information about the signs and symptoms of serious meningococcal infection
- make sure that you are vaccinated against serious infections caused by meningococcal bacteria and that you receive antibiotics if you need to start SOLIRIS right away and you are not up to date on your vaccines
- give you a Patient Safety Card about your risk of meningococcal infection, as discussed above

SOLIRIS may also increase the risk of other types of serious infections caused by encapsulated bacteria, including Streptococcus pneumoniae, Haemophilus influenzae, and Neisseria gonorrhoeae.

- If your child is treated with SOLIRIS, your child should receive vaccines against Streptococcus pneumoniae and Haemophilus influenzae type b (Hib).
- Certain people may be at risk of serious infections with gonorrhea. Talk to your healthcare provider about whether you are at risk for gonorrhea infection, about gonorrhea prevention, and regular testing.
- Certain fungal infections (aspergillus) may also happen if you take SOLIRIS and have a weak immune system or a low white blood cell count.

For more information about side effects, see "What are the possible side effects of SOLIRIS?"

What is SOLIRIS?
SOLIRIS is a prescription medicine used to treat:

- people with paroxysmal nocturnal hemoglobinuria (PNH).
- people with atypical hemolytic uremic syndrome (aHUS).
  SOLIRIS is not for use in treating people with Shiga toxin E. coli related hemolytic uremic syndrome (STEC-HUS).
- people 6 years of age and older with generalized myasthenia gravis (gMG) who are anti-acetylcholine receptor (AChR) antibody positive.
- adults with neuromyelitis optica spectrum disorder (NMOSD) who are anti-aquaporin-4 (AQP4) antibody positive.

It is not known if SOLIRIS is safe and effective in children with PNH or NMOSD.
It is not known if SOLIRIS is safe and effective in children with gMG below 6 years of age.

Who should not receive SOLIRIS?
Do not receive SOLIRIS if you have a serious meningococcal infection when you are starting SOLIRIS treatment.

Before you receive SOLIRIS, tell your healthcare provider about all of your medical conditions, including if you:

- have an infection or fever.
- are pregnant or plan to become pregnant. It is not known if SOLIRIS will harm your unborn baby.
- are breastfeeding or plan to breastfeed. It is not known if SOLIRIS passes into your breast milk.

Tell your healthcare provider about all the medicines you take, including prescription and over-the-counter medicines, vitamins, and herbal supplements. SOLIRIS and other medicines can affect each other causing side effects.
Know the medications you take and the vaccines you receive. Keep a list of them to show your healthcare provider and pharmacist when you get a new medicine.

How should I receive SOLIRIS?

- Your healthcare provider will give you SOLIRIS into your vein through an intravenous (IV) line usually over 35 minutes in adults and 1 to 4 hours in children.
- Adults will usually receive a SOLIRIS infusion:
  - weekly for 5 weeks, then
  - every 2 weeks.
- Children less than 18 years of age, your healthcare provider will decide how often you will receive SOLIRIS depending on your age and body weight.
- After each infusion, you should be monitored for at least 1 hour for infusion-related reactions. See "What are the possible side effects of SOLIRIS?" If you have an infusion-related reaction during your SOLIRIS infusion, your healthcare provider may decide to give SOLIRIS more slowly or stop your infusion.
- If you miss a SOLIRIS infusion, call your healthcare provider right away.
- If you have PNH, your healthcare provider will need to monitor you closely for at least 8 weeks after stopping SOLIRIS. Stopping treatment with SOLIRIS may cause breakdown of your red blood cells due to PNH.
  Symptoms or problems that can happen due to red blood cell breakdown include:

- drop in the number of your red blood cell count
- kidney problems

- drop in your platelet counts
- blood clots

- confusion
- difficulty breathing
- chest pain

- If you have aHUS, your healthcare provider will need to monitor you closely for at least 12 weeks after stopping SOLIRIS for signs of worsening aHUS symptoms or problems related to abnormal clotting (thrombotic microangiopathy).
  Symptoms or problems that can happen with abnormal clotting may include:

- stroke
- difficulty breathing

- confusion
- kidney problems

- seizure
- swelling in arms or legs

- chest pain (angina)
- a drop in your platelet count

What are the possible side effects of SOLIRIS?
SOLIRIS can cause serious side effects including:

- See "What is the most important information I should know about SOLIRIS?"
- Serious infusion-related reactions. Serious infusion-related reactions can happen during your SOLIRIS infusion. Tell your healthcare provider or nurse right away if you get any of these symptoms during your SOLIRIS infusion:
  - chest pain
  - trouble breathing or shortness of breath
  - swelling of your face, tongue, or throat
  - feel faint or pass out

If you have an infusion-related reaction to SOLIRIS, your healthcare provider may need to infuse SOLIRIS more slowly or stop SOLIRIS. See "How should I receive SOLIRIS?"
The most common side effects in people with PNH treated with SOLIRIS include:

- headache
- pain or swelling of your nose or throat (nasopharyngitis)

- back pain
- nausea

The most common side effects in people with aHUS treated with SOLIRIS include:

- headache
- diarrhea
- high blood pressure (hypertension)
- common cold (upper respiratory infection

- stomach-area (abdominal pain)
- vomiting
- pain or swelling of your nose or throat (nasopharyngitis)

- low red blood cell count (anemia)
- cough
- swelling of legs or feet (peripheral edema

- nausea
- urinary tract infections
- fever

The most common side effects in people with gMG treated with SOLIRIS include:

- muscle and joint (musculoskeletal) pain

The most common side effects in people with NMOSD treated with SOLIRIS include:

- common cold (upper respiratory infection)
- pain or swelling of your nose or throat (nasopharyngitis)
- diarrhea
- back pain
- dizziness
- flu like symptoms (influenza) including fever, headache, tiredness, cough, sore throat, and body aches

- joint pain (arthralgia)
- throat irritation (pharyngitis)
- bruising (contusion)

Tell your healthcare provider about any side effect that bothers you or that does not go away. These are not all the possible side effects of SOLIRIS.
Call your doctor for medical advice about side effects. You may report side effects to FDA at 1-800-FDA-1088.

General information about the safe and effective use of SOLIRIS.
Medicines are sometimes prescribed for purposes other than those listed in a Medication Guide. You can ask your pharmacist or healthcare provider for information about SOLIRIS that is written for health professionals.

What are the ingredients in SOLIRIS?
Active ingredient: eculizumab
Inactive ingredients: polysorbate 80 (vegetable origin), sodium chloride, sodium phosphate dibasic, sodium phosphate monobasic, and Water for Injection
Manufactured by: Alexion Pharmaceuticals, Inc., 121 Seaport Boulevard, Boston, MA 02210 USA. US License Number 1743

This Medication Guide has been approved by the U.S. Food and Drug Administration.

Revised: 02/2025

PRINCIPAL DISPLAY PANEL - 30 mL Vial Carton

Rx only

NDC 25682-001-01

Soliris®
(eculizumab)
Injection

300 mg/30 mL
(10 mg/mL)

For Intravenous Use

Must be diluted prior to use.
One 30 mL Single-Dose Vial

ATTENTION: Dispense the
enclosed Medication
Guide to each patient.